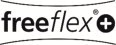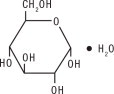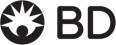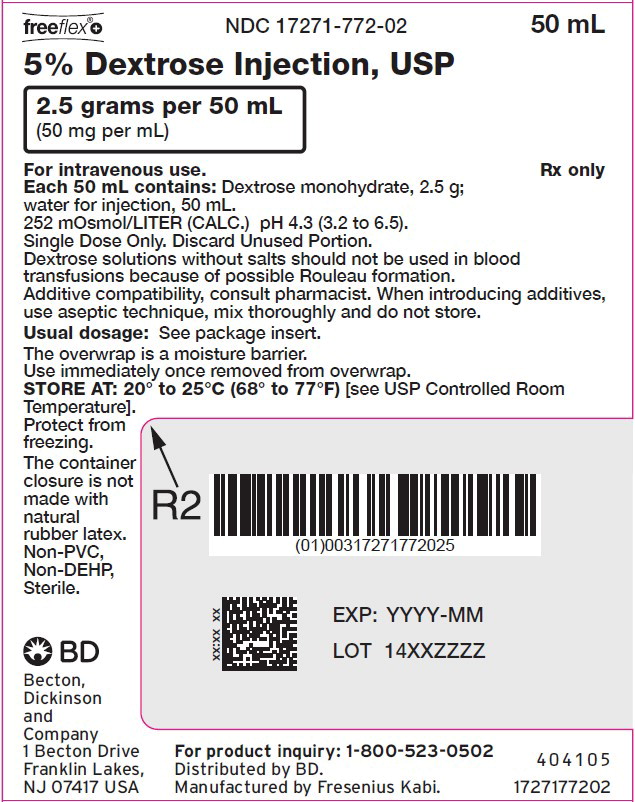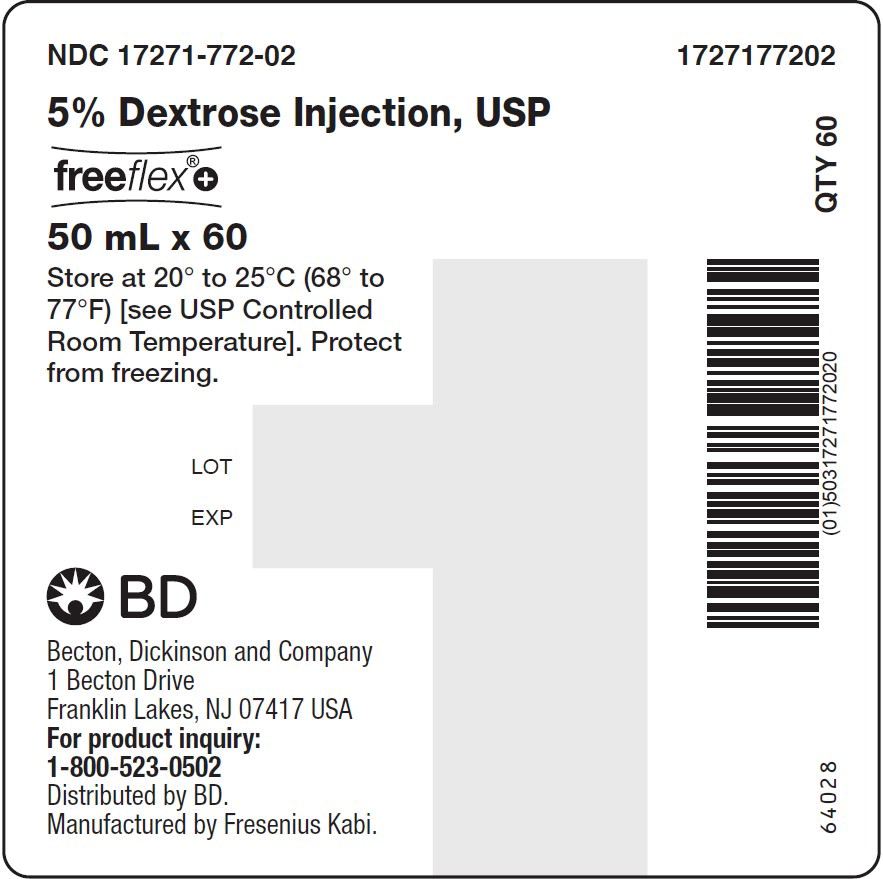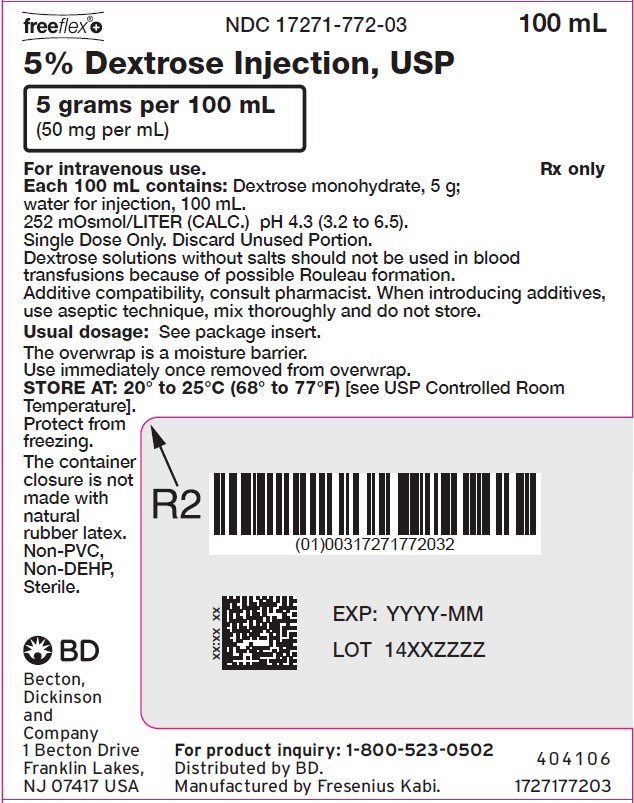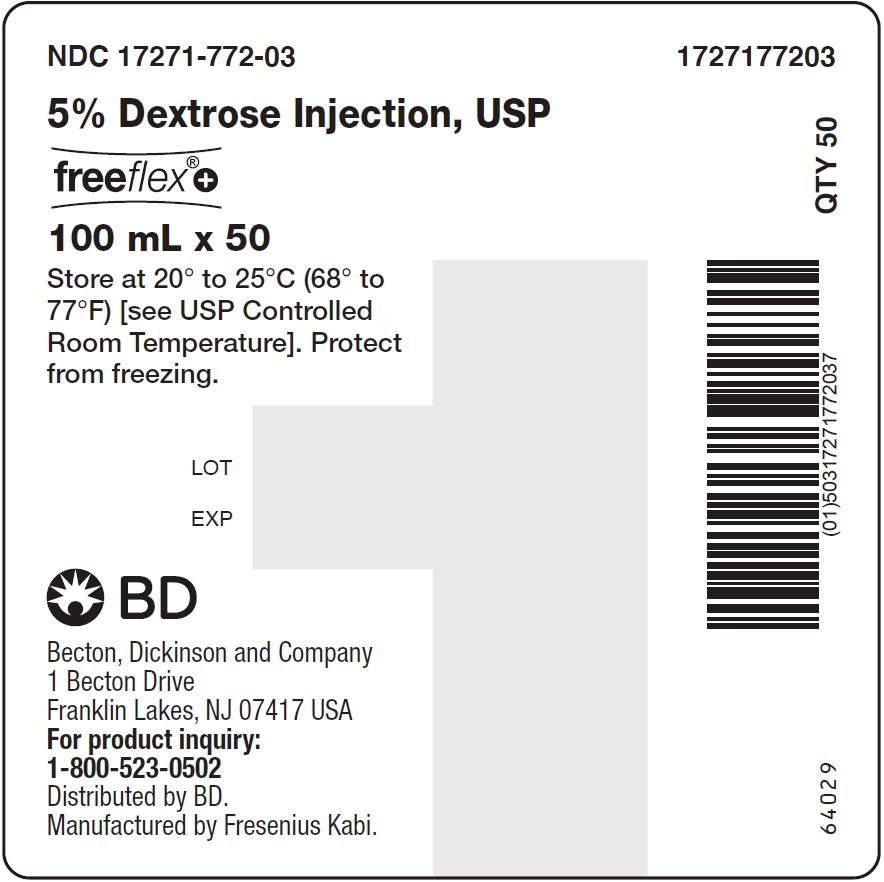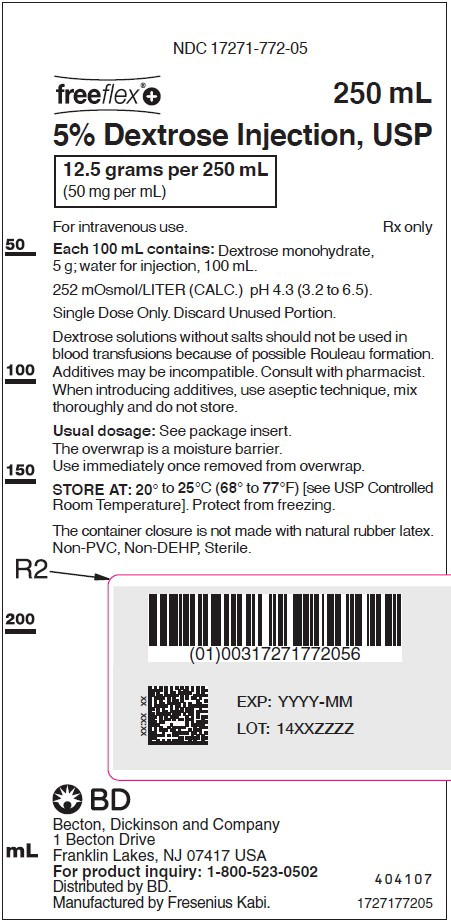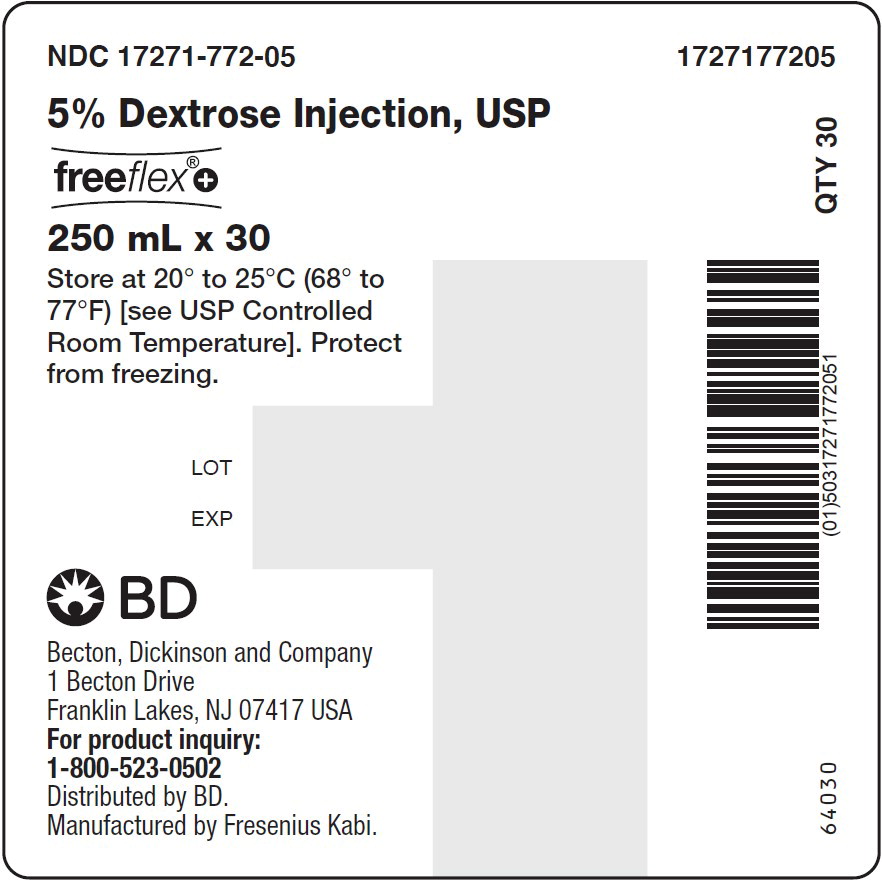 DRUG LABEL: Dextrose
NDC: 17271-772 | Form: INJECTION, SOLUTION
Manufacturer: BECTON DICKINSON AND COMPANY
Category: prescription | Type: HUMAN PRESCRIPTION DRUG LABEL
Date: 20260108

ACTIVE INGREDIENTS: DEXTROSE MONOHYDRATE 2500 mg/50 mL

5% Dextrose Injection, USP

Rx only

DESCRIPTION:

5% Dextrose Injection, USP solution is sterile and nonpyrogenic. It is a parenteral solution containing dextrose in water for injection intended for intravenous administration.

Each 100 mL of 5% Dextrose Injection, USP, contains dextrose monohydrate, 5 g in water for injection. The caloric value is 170 kcal/L. The osmolarity is 252 mOsmol/L (calc.), which is slightly hypotonic.

The solution pH is 4.3 (3.2 to 6.5).

This solution contains no bacteriostat, antimicrobial agent or added buffer and is intended only as a single-dose injection. When smaller doses are required the unused portion should be discarded.

5% Dextrose Injection, USP is a parenteral fluid and nutrient replenisher.

Dextrose, USP is chemically designated D-glucose monohydrate (C 6H 12O 6 • H 2O), a hexose sugar freely soluble in water. It has the following structural formula:

Water for Injection, USP is chemically designated H 2O.

The flexible container is fabricated from a specially formulated non-plasticized film containing polypropylene and thermoplastic elastomers (freeflex® bag). The freeflex® + bag has a needle-free injection port and can accept standard luer lock syringes to add medication. The amount of water that can permeate from the container into the overwrap is insufficient to affect the solution significantly. Solutions in contact with the flexible container can leach out certain of the container's chemical components in very small amounts within the expiration period. The suitability of the container material has been confirmed by tests in animals according to USP biological tests for plastic containers.

CLINICAL PHARMACOLOGY:

When administered intravenously, these solutions provide a source of water and carbohydrate.

Isotonic and hypertonic concentrations of dextrose are suitable for parenteral maintenance of water requirements when salt is not needed or should be avoided.

Solutions containing carbohydrate in the form of dextrose restore blood glucose levels and provide calories. Carbohydrate in the form of dextrose may aid in minimizing liver glycogen depletion and exerts a protein- sparing action. Dextrose injected parenterally undergoes oxidation to carbon dioxide and water.

Water is an essential constituent of all body tissues and accounts for approximately 70% of total body weight. Average normal adult daily requirements range from two to three liters (1 to 1.5 liters each for insensible water loss by perspiration and urine production).

Water balance is maintained by various regulatory mechanisms. Water distribution depends primarily on the concentration of electrolytes in the body compartments and sodium (Na ^+) plays a major role in maintaining physiologic equilibrium.

INDICATIONS AND USAGE:

Intravenous solutions containing dextrose are indicated for parenteral replenishment of fluid and minimal carbohydrate calories as required by the clinical condition of the patient.

CONTRAINDICATIONS:

5% Dextrose Injection, USP without electrolytes should not be administered simultaneously with blood through the same infusion set because of the possibility that pseudoagglutination of red cells may occur.

WARNINGS:

Excessive administration of potassium-free solutions may result in significant hypokalemia. The intravenous administration of these solutions can cause fluid and/or solute overloading resulting in dilution of serum electrolyte concentrations, overhydration, congested states or pulmonary edema.

The risk of dilutional states is inversely proportional to the electrolyte concentrations of administered parenteral solutions. The risk of solute overload causing congested states with peripheral and pulmonary edema is directly proportional to the electrolyte concentrations of such solutions.

PRECAUTIONS:

Clinical evaluation and periodic laboratory determinations are necessary to monitor changes in fluid balance, electrolyte concentrations and acid-base balance during prolonged parenteral therapy or whenever the condition of the patient warrants such evaluation.

Solutions containing dextrose should be used with caution in patients with known subclinical or overt diabetes mellitus.

Do not administer unless solution is clear and container is undamaged. Discard unused portion.

Carcinogenesis, Mutagenesis, Impairment of Fertility

Studies with 5% Dextrose Injection, USP have not been performed to evaluate carcinogenic potential, mutagenic potential or effects on fertility.

Pregnancy

Teratogenic Effects

Pregnancy Category C. Animal reproduction studies have not been conducted with dextrose. It is also not known whether dextrose can cause fetal harm when administered to a pregnant woman or can affect reproduction capacity. Dextrose should be given to a pregnant woman only if clearly needed.

Nursing Mothers

Caution should be exercised when 5% Dextrose Injection, USP is administered to a nursing mother.

Pediatric Use

The safety and effectiveness in the pediatric population are based on the similarity of the clinical conditions of the pediatric and adult populations. In neonates or very small infants the volume of fluid may affect fluid and electrolyte balance.

Frequent monitoring of serum glucose concentrations is required when dextrose is prescribed to pediatric patients, particularly neonates and low birth weight infants.

In very low birth weight infants, excessive or rapid administration of dextrose injection may result in increased serum osmolarity and possible intracerebral hemorrhage.

Geriatric Use

An evaluation of current literature revealed no clinical experience identifying differences in response between elderly and younger patients. In general, dose selection for an elderly patient should be cautious, usually starting at the low end of the dosing range, reflecting the greater frequency of decreased hepatic, renal, or cardiac function, and of concomitant disease or other drug therapy.

ADVERSE REACTIONS:

Reactions which may occur because of the solution or the technique of administration include febrile response, infection at the site of injection, venous thrombosis or phlebitis extending from the site of injection, extravasation and hypervolemia.

If an adverse reaction does occur, discontinue the infusion, evaluate the patient, institute appropriate therapeutic countermeasures and save the remainder of the fluid for examination if deemed necessary.

OVERDOSAGE:

In the event of overhydration or solute overload, re-evaluate the patient and institute appropriate corrective measures (see WARNINGS, PRECAUTIONS, and ADVERSE REACTIONS).

DOSAGE AND ADMINISTRATION:

The dose is dependent upon the age, weight and clinical condition of the patient.

As reported in the literature, the dosage and constant infusion rate of intravenous dextrose must be selected with caution in pediatric patients, particularly neonates and low birth weight infants, because of the increased risk of hyperglycemia/hypoglycemia.

Drug Interactions

Additives may be incompatible. Consult with pharmacist, if available. When introducing additives, use aseptic technique, mix thoroughly and do not store.

Parenteral drug products should be inspected visually for particulate matter and discoloration prior to administration, whenever solution and container permit (see PRECAUTIONS).

INSTRUCTIONS FOR USE:

Check flexible container solution composition, lot number, and expiry date.

Do not remove solution container from its overwrap until immediately before use.

Use sterile equipment and aseptic technique.

To Open

1. Turn solution container over so that the text is face down. Using the pre-cut corner tabs, peel open the overwrap and remove solution container.
2. Check the solution container for leaks by squeezing firmly. If leaks are found, or if the seal is not intact, discard the solution.
3. Do not use if the solution is cloudy or a precipitate is present.

To Add Medication

The Additive port of the freeflex® + container accepts standard luer lock syringes. Do not use a needle for additions.

1. Identify LIGHT BLUE Additive Port with arrow pointing toward solution container.
2. Immediately before injecting additives, break off LIGHT BLUE Additive Port Cap with the arrow pointing toward solution container.
3. Hold base of LIGHT BLUE Additive Port.
4. Attach Luer Lock syringe to the threaded LIGHT BLUE Additive Port. Inject additive.
5. Mix solution container contents thoroughly.

Preparation for Administration

1. Immediately before inserting the infusion set, break off BLUE Infusion Port Cap with the arrow pointing away from container.
2. Use a non-vented infusion set or close the air-inlet on a vented set.
3. Close the roller clamp of the infusion set.
4. Hold the base of BLUE Infusion Port.
5. Insert spike through BLUE Infusion Port by rotating wrist slightly until the spike is inserted.

NOTE: See full directions accompanying administration set.

WARNING: Do not use flexible container in series connections.

HOW SUPPLIED:

5% Dextrose Injection, USP is supplied in single dose flexible plastic containers as follows:

Product Code | Unit of Sale | Strength (Concentration) | Each
1727177202 | NDC 17271-772-02 Package of 60 freeflex® + bags | 2.5 grams per 50 mL (50 mg per mL) | NDC 17271-772-02 50 mL in a 100 mL freeflex® + bag
1727177203 | NDC 17271-772-03 Package of 50 freeflex® + bags | 5 grams per 100 mL (50 mg per mL) | NDC 17271-772-03 100 mL freeflex® + bag
1727177205 | NDC 17271-772-05 Package of 30 freeflex® + bags | 12.5 grams per 250 mL (50 mg per mL) | NDC 17271-772-05 250 mL freeflex® + bag

Store at 20° to 25°C (68° to 77°F) [see USP Controlled Room Temperature].

Exposure of pharmaceutical products to heat should be minimized. Avoid excessive heat. Protect from freezing.

The container closure is not made with natural rubber latex. Non-PVC, Non-DEHP, Sterile.

Becton, Dickinson and Company
1 Becton Drive
Franklin Lakes, NJ 07417 USA
For product inquiry: 1-800-523-0502

Distributed by BD.
Manufactured by Fresenius Kabi.

451834

Issued: August 2024

PACKAGE LABEL

PACKAGE LABEL - PRINCIPAL DISPLAY – 5% Dextrose 50 mL Bag Label

freeflex®+ NDC 17271-772-02 50 mL

5% Dextrose Injection, USP

2.5 grams per 50 mL

(50 mg per mL)
For intravenous use. Rx only

PACKAGE LABEL

PACKAGE LABEL - PRINCIPAL DISPLAY – 5% Dextrose 50 mL Case Label

NDC 17271-772-02 1727177202

5% Dextrose Injection, USP

freeflex®+

50 mL x 60

Store at 20° to 25°C (68° to 77°F)

[see USP Controlled Room Temperature].

Protect from freezing.

PACKAGE LABEL

PACKAGE LABEL - PRINCIPAL DISPLAY – 5% Dextrose 100 mL Bag Label

freeflex®+ NDC 17271-772-03 100 mL

5% Dextrose Injection, USP

5 grams per 100 mL

(50 mg per mL)
For intravenous use. Rx only

PACKAGE LABEL

PACKAGE LABEL - PRINCIPAL DISPLAY – 5% Dextrose 100 mL Case Label

NDC 17271-772-03 1727177203

5% Dextrose Injection, USP

freeflex®+

100 mL x 50

Store at 20° to 25°C (68° to 77°F)

[see USP Controlled Room Temperature].

Protect from freezing.

PACKAGE LABEL

PACKAGE LABEL - PRINCIPAL DISPLAY – 5% Dextrose 250 mL Bag Label

NDC 17271-772-05

freeflex®+ 250 mL

5% Dextrose Injection, USP

12.5 grams per 250 mL

(50 mg per mL)
For intravenous use. Rx only

PACKAGE LABEL

PACKAGE LABEL - PRINCIPAL DISPLAY – 5% Dextrose 250 mL Case Label

NDC 17271-772-05 1727177205

5% Dextrose Injection, USP

freeflex®+

250 mL x 30

Store at 20° to 25°C (68° to 77°F)

[see USP Controlled Room Temperature].

Protect from freezing.